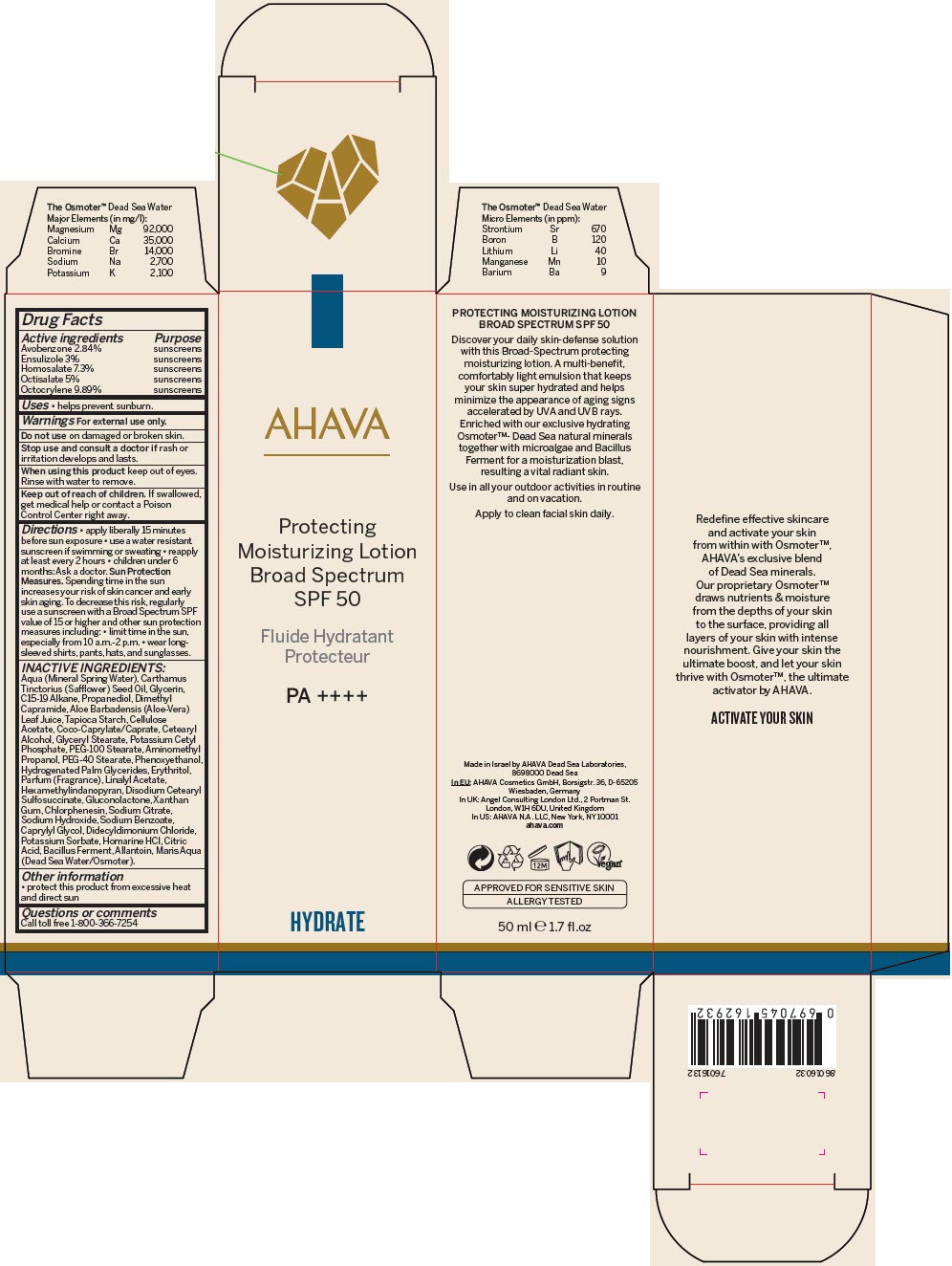 DRUG LABEL: AHAVA Protecting Moisturizing SPF50
NDC: 60289-307 | Form: LOTION
Manufacturer: AHAVA - Dead Sea Laboratories Ltd
Category: otc | Type: HUMAN OTC DRUG LABEL
Date: 20241216

ACTIVE INGREDIENTS: Avobenzone 0.0284 g/1 mL; Ensulizole 0.03 g/1 mL; Homosalate 0.073 g/1 mL; Octisalate 0.05 g/1 mL; Octocrylene 0.0989 g/1 mL
INACTIVE INGREDIENTS: Water; Safflower Oil; Glycerin; C15-19 Alkane; Propanediol; Dimethyl Capramide; Aloe Vera Leaf; Starch, Tapioca; Cellulose Acetate; Cocoyl Caprylocaprate; Cetostearyl Alcohol; Glyceryl Monostearate; Potassium Cetyl Phosphate; PEG-100 Stearate; Aminomethylpropanol; PEG-40 Monostearate; Phenoxyethanol; Hydrogenated Palm Glycerides; Erythritol; Linalyl Acetate; Hexamethylindanopyran; Gluconolactone; Xanthan Gum; Chlorphenesin; Sodium Citrate, Unspecified Form; Sodium Hydroxide; Sodium Benzoate; Caprylyl Glycol; Didecyldimonium Chloride; Potassium Sorbate; Homarine Hydrochloride; Citric Acid Monohydrate; Allantoin

AHAVA Protecting Moisturizing SPF50

Drug Facts

ACTIVE INGREDIENT

Active ingredients | Purpose
Avobenzone 2.84% | sunscreens
Ensulizole 3% | sunscreens
Homosalate 7.3% | sunscreens
Octisalate 5% | sunscreens
Octocrylene 9.89% | sunscreens

Uses

- helps prevent sunburn.

Warnings

For external use only.

Do not use on damaged or broken skin.

Stop use and consult a doctor if rash or irritation develops and lasts.

When using this product keep out of eyes. Rinse with water to remove.

Keep out of reach of children. If swallowed, get medical help or contact a Poison Control Center right away.

Directions

- apply liberally 15 minutes before sun exposure
- use a water resistant sunscreen if swimming or sweating
- reapply at least every 2 hours
- children under 6 months: Ask a doctor.

Sun Protection Measures. Spending time in the sun increases your risk of skin cancer and early skin aging. To decrease this risk, regularly use a sunscreen with a Broad Spectrum SPF value of 15 or higher and other sun protection measures including:

- limit time in the sun, especially from 10 a.m.-2 p.m.
- wear long-sleeved shirts, pants, hats, and sunglasses.

INACTIVE INGREDIENTS

Aqua (Mineral Spring Water), Carthamus Tinctorius (Safflower) Seed Oil, Glycerin, C15-19 Alkane, Propanediol, Dimethyl Capramide, Aloe Barbadensis (Aloe-Vera) Leaf Juice, Tapioca Starch, Cellulose Acetate, Coco-Caprylate/Caprate, Cetearyl Alcohol, Glyceryl Stearate, Potassium Cetyl Phosphate, PEG-100 Stearate, Aminomethyl Propanol, PEG-40 Stearate, Phenoxyethanol, Hydrogenated Palm Glycerides, Erythritol, Parfum (Fragrance), Linalyl Acetate, Hexamethylindanopyran, Disodium Cetearyl Sulfosuccinate, Gluconolactone, Xanthan Gum, Chlorphenesin, Sodium Citrate, Sodium Hydroxide, Sodium Benzoate, Caprylyl Glycol, Didecyldimonium Chloride, Potassium Sorbate, Homarine HCl, Citric Acid, Bacillus Ferment, Allantoin, Maris Aqua (Dead Sea Water/Osmoter).

Other information

- protect this product from excessive heat and direct sun

Questions or comments

Call toll free 1-800-366-7254

PRINCIPAL DISPLAY PANEL - 50 ml Tube Carton

AHAVA

Protecting
Moisturizing Lotion
Broad Spectrum
SPF 50

PA ++++

HYDRATE